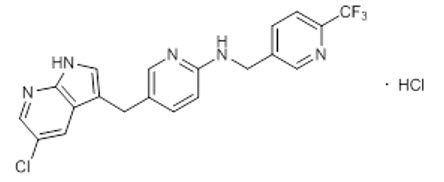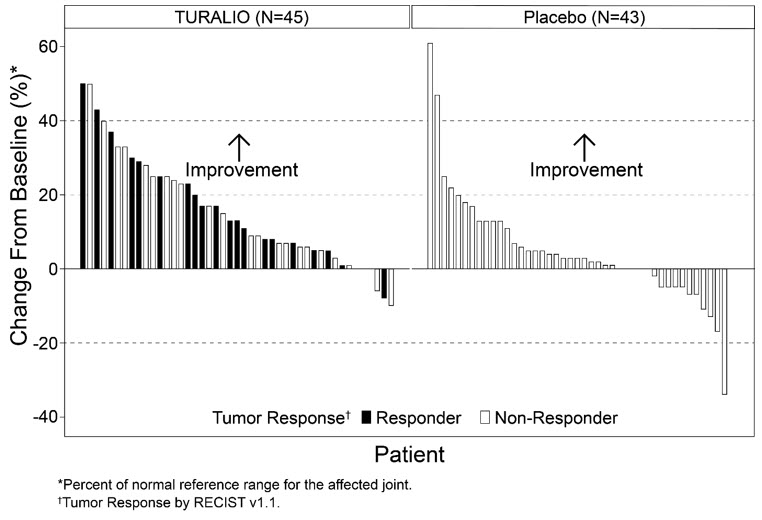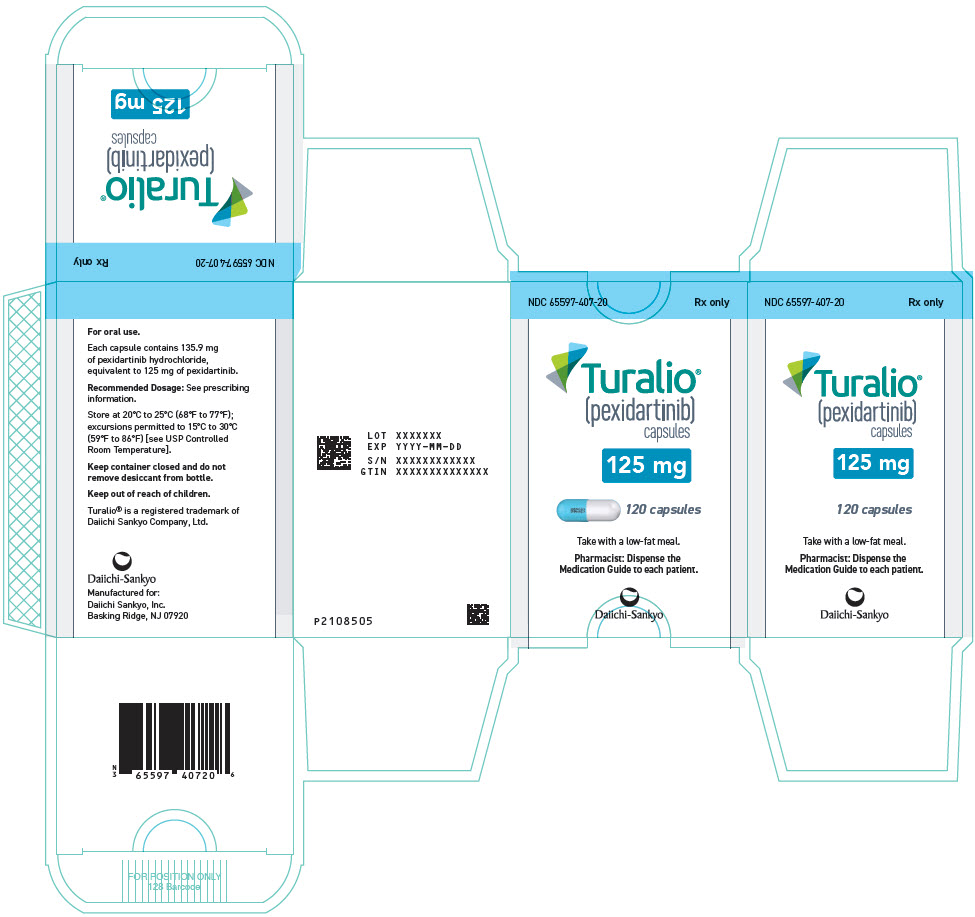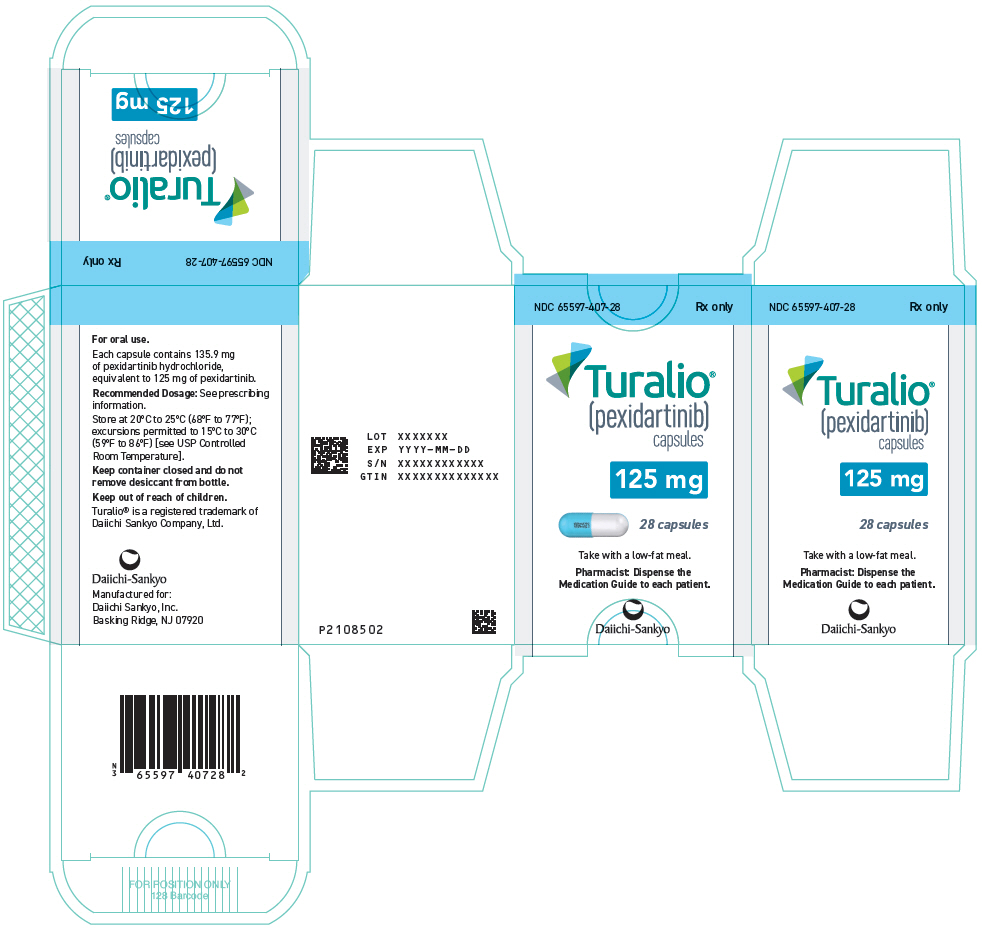 DRUG LABEL: Turalio
NDC: 65597-407 | Form: CAPSULE
Manufacturer: Daiichi Sankyo Inc.
Category: prescription | Type: HUMAN PRESCRIPTION DRUG LABEL
Date: 20250116

ACTIVE INGREDIENTS: PEXIDARTINIB HYDROCHLORIDE 125 mg/1 1
INACTIVE INGREDIENTS: POLOXAMER 407; MANNITOL; CROSPOVIDONE, UNSPECIFIED; MAGNESIUM STEARATE; HYPROMELLOSE, UNSPECIFIED; TITANIUM DIOXIDE; FD&C BLUE NO. 1

HIGHLIGHTS OF PRESCRIBING INFORMATION

These highlights do not include all the information needed to use TURALIO safely and effectively. See full prescribing information for TURALIO.
TURALIO® (pexidartinib) capsules, for oral use
Initial U.S. Approval: 2019

WARNING: HEPATOTOXICITY

See full prescribing information for complete boxed warning.

- TURALIO can cause serious and potentially fatal liver injury, including vanishing bile duct syndrome. (5.1)
- Monitor liver tests prior to initiation of TURALIO and at specified intervals during treatment. Withhold and dose reduce or permanently discontinue TURALIO based on severity of hepatotoxicity. Monitoring and prompt cessation of TURALIO may not eliminate the risk of serious and potentially fatal liver injury. (2.2, 5.1)
- TURALIO is available only through a restricted program called the TURALIO Risk Evaluation and Mitigation Strategy (REMS) Program. (5.2)

RECENT MAJOR CHANGES

Boxed Warning | 1/2025
Warnings and Precautions (5.1) | 1/2025

1 INDICATIONS AND USAGE

TURALIO is a kinase inhibitor indicated for the treatment of adult patients with symptomatic tenosynovial giant cell tumor (TGCT) associated with severe morbidity or functional limitations and not amenable to improvement with surgery. (1)

2 DOSAGE AND ADMINISTRATION

- Recommended Dosage: 250 mg orally twice daily with a low-fat meal (approximately 11 to 14 grams of total fat). (2.1)
- See full prescribing information for dosage modifications due to adverse reactions, renal impairment and hepatic impairment. (2.2, 2.5, 2.6)

3 DOSAGE FORMS AND STRENGTHS

Capsules: 125 mg (3)

4 CONTRAINDICATIONS

None. (4)

5 WARNINGS AND PRECAUTIONS

- Embryo-Fetal Toxicity: May cause fetal harm. Advise patients of reproductive potential of the potential risk to a fetus and to use an effective non-hormonal method of contraception. (5.3, 7.3, 8.1, 8.3)
- Potential Risks Associated with a High-Fat Meal: May increase incidence and severity of adverse reactions, including hepatotoxicity. Avoid taking TURALIO with a high-fat meal (approximately 55 to 65 grams of total fat). (2.1, 5.4)

6 ADVERSE REACTIONS

Most common adverse reactions (>20%) were increased lactate dehydrogenase, increased aspartate aminotransferase, hair color changes, fatigue, increased alanine aminotransferase, decreased neutrophils, increased cholesterol, increased alkaline phosphatase, decreased lymphocytes, eye edema, decreased hemoglobin, rash, dysgeusia, and decreased phosphate. (6.1)

To report SUSPECTED ADVERSE REACTIONS, contact Daiichi Sankyo, Inc. at 1-877-437-7763 or FDA at 1-800-FDA-1088 or www.fda.gov/medwatch.

7 DRUG INTERACTIONS

- Use with Hepatotoxic Products: Avoid coadministration of TURALIO with other products known to cause hepatotoxicity. (7.1)
- Moderate or Strong CYP3A Inhibitors: Reduce the dose of TURALIO if concomitant use of moderate or strong CYP3A inhibitors cannot be avoided. (2.3, 7.2)
- Strong CYP3A Inducers: Avoid concomitant use of strong CYP3A inducers. (7.2)
- UGT Inhibitors: Reduce the dose of TURALIO if concomitant use of UGT inhibitors cannot be avoided. (2.3, 7.2)
- Acid-Reducing Agents: Avoid concomitant use of proton pump inhibitors. Use histamine-2 receptor antagonists or antacids if needed. (2.4, 7.2)
- High-Fat Meal: Avoid taking TURALIO with a high-fat meal. (2.1, 5.4, 7.2).
- CYP3A Substrates: Avoid concomitant use with CYP3A substrates where minimal concentration changes may lead to serious therapeutic failure. (7.3)

8 USE IN SPECIFIC POPULATIONS

- Lactation: Advise not to breastfeed. (8.2)
- Renal Impairment: Reduce the dosage for patients with mild to severe renal impairment. (2.5, 8.6)
- Hepatic Impairment: Reduce the dosage for patients with moderate hepatic impairment. (2.6, 8.7)

FULL PRESCRIBING INFORMATION

WARNING: HEPATOTOXICITY

- TURALIO can cause serious and potentially fatal liver injury, including vanishing bile duct syndrome [see Warnings and Precautions (5.1)].
- Monitor liver tests prior to initiation of TURALIO and at specified intervals during treatment. Withhold and dose reduce or permanently discontinue TURALIO based on severity of hepatotoxicity. Monitoring and prompt cessation of TURALIO may not eliminate the risk of serious and potentially fatal liver injury [see Dosage and Administration (2.2), Warnings and Precautions (5.1)].
- TURALIO is available only through a restricted program called the TURALIO Risk Evaluation and Mitigation Strategy (REMS) Program [see Warnings and Precautions (5.2)].

1 INDICATIONS AND USAGE

TURALIO is indicated for the treatment of adult patients with symptomatic tenosynovial giant cell tumor (TGCT) associated with severe morbidity or functional limitations and not amenable to improvement with surgery.

2 DOSAGE AND ADMINISTRATION

2.1 Recommended Dosage

The recommended dosage of TURALIO is 250 mg taken orally twice daily with a low-fat meal (approximately 11 to 14 grams of total fat) until disease progression or unacceptable toxicity [see Clinical Pharmacology (12.3)]. Taking TURALIO with a high-fat meal (approximately 55 to 65 grams of total fat) increases pexidartinib concentrations and may increase the risk of adverse reactions, including hepatotoxicity [see Warnings and Precautions (5.1, 5.4), Drug Interactions (7.2), Clinical Pharmacology (12.2, 12.3)].

Swallow TURALIO capsules whole. Do not open, break, or chew the capsules.

If a patient vomits or misses a dose of TURALIO, instruct the patient to take the next dose at its scheduled time.

2.2 Dosage Modifications for Adverse Reactions

The recommended dose reductions for adverse reactions are provided in Table 1.

Table 1: Recommended Dose Reductions for TURALIO for Adverse Reactions
Dose Reduction | Total Daily Dose | Administration of Total Daily Dose with Low-Fat Meal
First | 375 mg | 125 mg in the morning and 250 mg in the evening
Second | 250 mg | 125 mg twice daily

Permanently discontinue TURALIO in patients who are unable to tolerate 125 mg orally twice daily.

The recommended dosage modifications for adverse reactions are summarized in Table 2.

Table 2: Recommended Dosage Modifications for TURALIO for Adverse Reactions
Adverse Reaction | Severity | TURALIO Dosage Modifications
Hepatotoxicity [see Warnings and Precautions (5.1)]
Increased ALT and/or AST | Greater than 3 to 5 times ULN | - Withhold and monitor liver tests weekly. - If AST and ALT are less than or equal to 3 times ULN within 4 weeks, resume at reduced dose. - If AST or ALT is not less than or equal to 3 times ULN in 4 weeks, permanently discontinue TURALIO.
Increased ALT and/or AST | Greater than 5 to 10 times ULN | - Withhold and monitor liver tests twice weekly. - If AST and ALT are less than or equal to 3 times ULN within 4 weeks, resume at reduced dose. - If AST or ALT is not less than or equal to 3 times ULN in 4 weeks, permanently discontinue TURALIO.
Increased ALT and/or AST | Greater than 10 times ULN | - Permanently discontinue TURALIO. - Monitor liver tests twice weekly until AST or ALT is less than or equal to 5 times ULN, then weekly until less than or equal to 3 times ULN.
Increased ALP [Confirm ALP elevations as liver isozyme fraction.] and GGT | ALP greater than 2 times ULN with GGT greater than 2 times ULN | - Permanently discontinue TURALIO. Monitor liver tests twice weekly until ALP is less than or equal to 5 times ULN, then weekly until less than or equal to 2 times ULN.
Increased bilirubin | TB greater than ULN to less than 2 times ULN or DB greater than ULN and less than 1.5 times ULN | - Withhold and monitor liver tests twice weekly. - If an alternate cause for increased bilirubin is confirmed and bilirubin is less than ULN within 4 weeks, resume at reduced dose. - If bilirubin is not less than ULN in 4 weeks, permanently discontinue TURALIO.
Increased bilirubin | TB greater or equal to 2 times ULN or DB greater than 1.5 times ULN | - Permanently discontinue TURALIO. - Monitor liver tests twice weekly until bilirubin is less than or equal to ULN.
Adverse Reactions or Other Laboratory Abnormalities [see Adverse Reactions (6.1)]
Any | Severe or intolerable | - Withhold until improvement or resolution. - Resume at a reduced dose upon improvement or resolution.
ALT = alanine aminotransferase; ALP = alkaline phosphatase; AST = aspartate aminotransferase; DB = direct bilirubin; GGT = gamma-glutamyl transferase; TB = total bilirubin; ULN = upper limit of normal

2.3 Concomitant Use of Moderate or Strong CYP3A Inhibitors or UGT Inhibitors

Avoid concomitant use of TURALIO with moderate or strong CYP3A inhibitors or UGT inhibitors during treatment with TURALIO. If concomitant use with a moderate or strong CYP3A inhibitor or UGT inhibitor cannot be avoided, reduce the TURALIO dose according to the recommendations in Table 3.

If concomitant use of a moderate or strong CYP3A inhibitor or UGT inhibitor is discontinued, increase the TURALIO dose (after 3 plasma half-lives of the moderate or strong CYP3A inhibitor or UGT inhibitor) to the dose that was used before starting the inhibitor [see Clinical Pharmacology (12.3)].

Table 3: Recommended Dosage Reductions for TURALIO for Concomitant Use of Moderate or Strong CYP3A Inhibitors or UGT Inhibitors
Total Daily Dose [The Total Daily Dose represents the recommended dose (row one) and the recommended dose after modifications due to adverse reactions, renal impairment, or moderate hepatic impairment (rows two and three) [see Dosage and Administration (2.2, 2.5, 2.6)].] | Modified Total Daily Dose for Concomitant Use with Moderate or Strong CYP3A Inhibitors or UGT Inhibitors | Dosing Schedule for Modified Total Daily Dose for Use with Moderate or Strong CYP3A Inhibitors or UGT Inhibitors
 |  | Administer with Low-Fat Meal
500 mg | 250 mg | 125 mg twice daily
375 mg | 250 mg | 125 mg twice daily
250 mg | 125 mg | 125 mg once daily

2.4 Concomitant Use of Acid-Reducing Agents

Avoid the concomitant use of proton pump inhibitors (PPI) while taking TURALIO. As an alternative to a PPI, administer TURALIO 2 hours before or 2 hours after taking a locally-acting antacid, or if using a histamine 2 (H2)-receptor antagonist, administer TURALIO at least 2 hours before or 10 hours after taking an H2-receptor antagonist [see Clinical Pharmacology (12.3)].

2.5 Dosage Modification for Renal Impairment

The recommended dosage of TURALIO for patients with mild to severe renal impairment (creatinine clearance [CLcr] 15 to 89 mL/min estimated by Cockcroft-Gault using actual body weight) is 125 mg in the morning and 250 mg in the evening with a low-fat meal [see Clinical Pharmacology (12.3)].

2.6 Dosage Modification for Hepatic Impairment

The recommended dosage of TURALIO for patients with moderate hepatic impairment (total bilirubin >1.5 to 3 × upper limit of normal (ULN), not due to Gilbert's syndrome, with any AST) is 125 mg twice daily with a low-fat meal [see Clinical Pharmacology (12.3)]. TURALIO has not been studied in patients with severe hepatic impairment (total bilirubin >3 to 10 × ULN and any AST).

3 DOSAGE FORMS AND STRENGTHS

Capsules: 125 mg, size 1 with white opaque body and powder blue opaque cap with black print "DSC521"

4 CONTRAINDICATIONS

None.

5 WARNINGS AND PRECAUTIONS

5.1 Hepatotoxicity

TURALIO can cause serious and potentially fatal liver injury and is available only through a restricted program under a Risk Evaluation and Mitigation Strategy (REMS) [see Warnings and Precautions (5.2)].

Hepatotoxicity, including liver failure and life-threatening vanishing bile duct syndrome (VBDS), ductopenia, and symptomatic cholestasis (including severe pruritus) can occur in patients treated with TURALIO and can occur despite monitoring and prompt drug cessation. The mechanism of cholestatic hepatotoxicity is unknown and its occurrence cannot be predicted. It is unknown whether liver injury can also occur in the absence of increased transaminases.

Of the first 609 patients who received TURALIO under the REMS program, 32 (5.3%) developed a liver injury event of concern (LIEC), defined as any serious liver-related outcome or any liver abnormality that triggers drug discontinuation per the US Prescribing Information [see Dosage and Administration (2.2)]. These 32 patients developed liver toxicity within 71 days of the first dose of TURALIO; ten required hospitalization, and two developed VBDS. Sixteen of the 32 patients had not fully recovered at the time of the analysis, including 6 patients followed for at least 6 months after discontinuation.

Among 768 patients who received TURALIO in clinical trials, there were two irreversible cases of cholestatic liver injury. One patient with advanced cancer and ongoing liver toxicity died and one patient with a confirmed case of VBDS required a liver transplant.

In ENLIVEN, 3 of 61 (5%) patients who received TURALIO developed signs of serious liver injury, defined as ALT or AST ≥3 × ULN with total bilirubin ≥2 × ULN. In these patients, peak ALT ranged from 6 to 9 × ULN, peak total bilirubin ranged from 2.5 to 15 × ULN, and alkaline phosphatase (ALP) was ≥2 × ULN. ALT, AST, and total bilirubin improved to <2 × ULN in these three patients 1 to 7 months after discontinuing TURALIO.

Avoid TURALIO in patients with pre-existing increased serum transaminases; total bilirubin or direct bilirubin (>ULN); or active liver or biliary tract disease, including increased ALP. Monitor liver tests, including AST, ALT, total bilirubin, direct bilirubin, ALP, and gamma-glutamyl transferase (GGT) prior to initiation of TURALIO, weekly for the first 8 weeks, every 2 weeks for the next month and every 3 months thereafter. Withhold and dose reduce, or permanently discontinue TURALIO based on the severity of the hepatotoxicity [see Dosage and Administration (2.2)]. Refer patients to a hepatologist if liver tests do not return to normal. Rechallenge with a reduced dose of TURALIO may result in a recurrence of increased serum transaminases, bilirubin, ALP., or other signs of liver injury. Monitor liver tests weekly for the first month after rechallenge.

5.2 TURALIO REMS Program

TURALIO is only available through a restricted program under a REMS, because of the risk of hepatotoxicity [see Warnings and Precautions (5.1)].

Notable requirements of the TURALIO REMS Program include the following:

- Prescribers must be certified with the program by enrolling and completing training.
- Patients must complete and sign an enrollment form for inclusion in a patient registry.
- Pharmacies must be certified with the program and must only dispense to patients who are authorized to receive TURALIO.

Further information is available at www.TURALIOREMS.com or 1-833-887-2546.

5.3 Embryo-Fetal Toxicity

Based on animal studies and its mechanism of action, TURALIO may cause fetal harm when administered to a pregnant woman. Oral administration of pexidartinib to pregnant rats and rabbits during the period of organogenesis resulted in malformations, increased post-implantation loss, and abortion at exposures approximately equal to the human exposure at the recommended dose based on area under the curve (AUC).

Advise pregnant women of the potential risk to a fetus. Advise females of reproductive potential to use effective non-hormonal contraception, since TURALIO can render hormonal contraceptives ineffective, during treatment with TURALIO and for 1 month after the final dose. Advise males with female partners of reproductive potential to use effective contraception during treatment with TURALIO and for 1 week after the final dose [see Drug Interactions (7.3), Use in Specific Populations (8.1, 8.3)].

5.4 Potential Risks Associated with a High-Fat Meal

Taking TURALIO with a high-fat meal increases pexidartinib concentrations, which may increase the incidence and severity of adverse reactions, including hepatotoxicity [see Clinical Pharmacology (12.2, 12.3)].

Instruct patients to take TURALIO with a low-fat meal (approximately 11 to 14 grams of total fat) and to avoid taking TURALIO with a high-fat meal (approximately 55 to 65 grams of total fat). Consider referring patients to a dietician as deemed necessary [see Dosage and Administration (2.1), Warnings and Precautions (5.1), Drug Interactions (7.2)].

6 ADVERSE REACTIONS

The following clinically significant adverse reactions are described elsewhere in the labeling:

- Hepatotoxicity [see Warnings and Precautions (5.1)].

6.1 Clinical Trials Experience

Because clinical trials are conducted under widely varying conditions, adverse reaction rates observed in the clinical trials of a drug cannot be directly compared to rates in the clinical trials of another drug and may not reflect the rates observed in practice.

The safety of TURALIO 250 mg orally twice daily administered with a low-fat meal has been established based on adequate and well-controlled studies of TURALIO 400 mg orally twice daily administered on an empty stomach and additional pharmacokinetic data that indicate there is no clinically significant difference in the relative exposure between the two dosages [see Clinical Pharmacology (12.3)].

The safety of TURALIO was evaluated in ENLIVEN [see Clinical Studies (14.1)]. ENLIVEN excluded patients with ALT, AST, or total bilirubin >1.5 × ULN; and known active or chronic infection with hepatitis B or C virus, or human immunodeficiency virus. Patients received TURALIO without food at a dose of 400 mg in the morning and 600 mg in the evening orally for 2 weeks followed by 400 mg orally twice daily until disease progression or unacceptable toxicity. Seventy-nine percent of patients received TURALIO for 6 months or longer and 66% for greater than one year.

The median age of TURALIO-treated patients was 44 years (range: 22-75), 57% were females, and 85% were White.

Serious adverse reactions were reported in 13% of patients who received TURALIO. Most frequent (occurring in >1 patient) serious adverse reactions included abnormal liver tests (3.3%) and hepatotoxicity (3.3%).

Permanent discontinuation due to an adverse reaction occurred in 13% of patients who received TURALIO. Most frequent adverse reactions (occurring in >1 patient) requiring permanent discontinuation included increased ALT (4.9%), increased AST (4.9%) and hepatotoxicity (3.3%).

Dose reductions or interruptions occurred in 38% of patients who received TURALIO. Most frequent adverse reactions (occurring in >1 patient) requiring a dosage reduction or interruption were increased ALT (13%), increased AST (13%), nausea (8%), increased ALP (7%), vomiting (4.9%), increased bilirubin (3.3%), increased GGT (3.3%), dizziness (3.3%), and abdominal pain (3.3%).

The most common (>20%) adverse reactions, including laboratory abnormalities, in patients who received TURALIO were: increased lactate dehydrogenase (LDH), increased AST, hair color changes, fatigue, increased ALT, decreased neutrophils, increased cholesterol, increased ALP, decreased lymphocytes, eye edema, decreased hemoglobin, rash, dysgeusia, and decreased phosphate.

Tables 4, 5, and 6 summarize the adverse reactions and laboratory abnormalities in ENLIVEN during the randomized phase (Week 25).

Table 4: Adverse Reactions (≥10% All Grades or >2% Grade ≥ 3) in Patients Receiving TURALIO with a Difference Between Arms of >5% Compared to Placebo Through Week 25 in ENLIVEN
 | TURALIO N=61 |  | Placebo N=59
Adverse Reaction | All Grades (%) | Grade ≥ 3 (%) | All Grades (%) | Grade ≥ 3 (%)
Skin and subcutaneous tissue
Hair color changes | 67 | 0 | 3.4 | 0
Rash [Rash includes rash, maculo-papular rash, rash pruritic, urticaria, erythema, dermatitis acneiform, dermatitis allergic.] | 28 | 1.6 | 7 | 0
Pruritus [Pruritis includes pruritus, pruritus generalized.] | 18 | 0 | 3.4 | 0
General
Fatigue [Fatigue includes fatigue, asthenia, malaise.] | 64 | 0 | 41 | 0
Peripheral edema [Peripheral edema includes face edema, localized edema, edema peripheral, peripheral swelling.] | 20 | 0 | 7 | 0
Eye
Eye edema [Eye edema includes periorbital edema, eye edema, eyelid edema, papilledema.] | 30 | 1.6 | 5 | 0
Nervous system
Dysgeusia [Dysgeusia includes dysgeusia, ageusia.] | 26 | 0 | 1.7 | 0
Neuropathy [Neuropathy includes neuropathy peripheral, paresthesia, hypoesthesia, burning sensation.] | 10 | 0 | 5 | 0
Gastrointestinal
Vomiting | 20 | 1.6 | 5 | 0
Constipation | 12 | 0 | 5 | 0
Metabolism and nutrition
Decreased appetite | 16 | 0 | 10 | 0
Vascular
Hypertension | 15 | 4.9 | 10 | 0

Table 5: Hepatic Laboratory Abnormalities (≥10% All Grades or >2% Grade ≥ 3) Worsening from Baseline in Patients Receiving TURALIO with a Difference Between Arms of >5% Compared to Placebo Through Week 25 in ENLIVEN
 | TURALIO [Each test incidence is based on the number of patients who had both a baseline and at least one on-study measurement TURALIO (n=61) and placebo (n=59).] |  |  | Placebo
Laboratory Abnormality [Graded per NCI CTCAE v 4.03] | Grade 1 (%) | Grade 2 (%) | Grade ≥ 3 (%) | Grade 1 (%) | Grade 2 (%) | Grade ≥ 3 (%)
Liver Tests
Increased AST | 61 | 15 | 12 | 15 | 0 | 0
Increased ALT | 31 | 13 | 20 | 22 | 0 | 0
Increased ALP | 31 | 3.3 | 4.9 | 1.7 | 0 | 0
Increased bilirubin | 3.3 | 3.3 | 3.3 | 0 | 0 | 0
ALT = alanine aminotransferase; AST = aspartate aminotransferase; ALP = alkaline phosphatase

Table 6: Other Laboratory Abnormalities Worsening from Baseline (≥10% All Grades or >2% of Grade ≥ 3) in Patients Receiving TURALIO with a Difference Between Arms of >5% Compared to Placebo Through Week 25 in ENLIVEN
 | TURALIO [Each test incidence is based on the number of patients who had both a baseline and at least one on-study measurement TURALIO (n = 61) and placebo (n = 58-59).] |  | Placebo
Laboratory Abnormality [Graded per NCI CTCAE v 4.03 except for LDH] | All Grades (%) | Grade ≥3 (%) | All Grades (%) | Grade ≥3 (%)
Chemistry
Increased LDH [LDH: Grade 1 >ULN to ≤2.5 × ULN; Grade 2 >2.5 to ≤5 × ULN; Grade 3 >5 to ≤20 × ULN; Grade 4 >20 × ULN] | 92 | 0 | 5 | 0
Increased cholesterol | 44 | 4.9 | 25 | 0
Decreased phosphate | 25 | 3.3 | 5 | 0
Hematology
Decreased neutrophils | 44 | 3.3 | 9 | 0
Decreased lymphocytes | 38 | 1.6 | 3.4 | 0
Decreased hemoglobin | 30 | 0 | 14 | 1.7
Decreased platelets | 15 | 0 | 5 | 0
LDH=Lactate Dehydrogenase

Clinically relevant adverse reactions occurring in <10% of patients were:

Eye: blurred vision, photophobia, diplopia, reduced visual acuity

Gastrointestinal: dry mouth, stomatitis, mouth ulceration

General: pyrexia

Hepatobiliary: cholangitis, hepatotoxicity, liver disorder

Neurological: cognitive disorders (memory impairment, amnesia, confusional state, disturbance in attention, attention deficit/hyperactivity disorder)

Skin and subcutaneous tissue: alopecia, skin pigment changes (hypopigmentation, depigmentation, discoloration, hyperpigmentation), photosensitivity reactions.

6.2 Postmarketing Experience

The following adverse reactions have been identified during post-approval use of TURALIO. Because these reactions are reported voluntarily from a population of uncertain size, it is not always possible to reliably estimate their frequency or establish a causal relationship to drug exposure.

Investigations: Blood creatine phosphokinase increased

7 DRUG INTERACTIONS

7.1 Use with Hepatotoxic Products

TURALIO can cause hepatotoxicity. In patients with increased serum transaminases, total bilirubin, or direct bilirubin (>ULN) or active liver or biliary tract disease, avoid coadministration of TURALIO with other products known to cause hepatotoxicity [see Warnings and Precautions (5.1)].

7.2 Effect of Other Drugs or Food on TURALIO

Table 7: Effect of Other Drugs or Food on TURALIO
Moderate or Strong CYP3A Inhibitors
Clinical Impact | - Concomitant use of a moderate or strong CYP3A inhibitor may increase pexidartinib concentrations [see Clinical Pharmacology (12.3)], which may increase the incidence and severity of adverse reactions of TURALIO.
Management | - Reduce TURALIO dosage if concomitant use of moderate or strong CYP3A inhibitors, including grapefruit or grapefruit juice, cannot be avoided [see Dosage and Administration (2.3)].
Strong CYP3A Inducers
Clinical Impact | - Concomitant use of a strong CYP3A inducer decreases pexidartinib concentrations [see Clinical Pharmacology (12.3)], which may decrease the efficacy of TURALIO.
Management | - Avoid concomitant use of strong CYP3A inducers, including St John's wort.
UGT Inhibitors
Clinical Impact | - Concomitant use of a UGT inhibitor increases pexidartinib concentrations [see Clinical Pharmacology (12.3)], which may increase the incidence and severity of adverse reactions of TURALIO.
Management | - Reduce TURALIO dosage if concomitant use of UGT inhibitors cannot be avoided [see Dosage and Administration (2.3)].
Acid-Reducing Agents
Clinical Impact | - Concomitant use of a PPI decreases pexidartinib concentrations [see Clinical Pharmacology (12.3)], which may decrease the efficacy of TURALIO.
Management | - Avoid concomitant use of PPIs with TURALIO. As an alternative to PPIs, use locally-acting antacids or H2-receptor antagonists [see Dosage and Administration (2.4)].
High-Fat Meal
Clinical Impact | - Taking TURALIO with a high-fat meal increased pexidartinib concentrations [see Clinical Pharmacology (12.3)], which may increase the incidence and severity of TURALIO adverse reactions, including hepatotoxicity [see Warnings and Precautions (5.1, 5.4)].
Management | - Take TURALIO with a low-fat meal (approximately 11 to 14 grams of total fat). Avoid taking TURALIO with a high-fat meal (approximately 55 to 65 grams of total fat) [see Dosage and Administration (2.1)].

7.3 Effect of TURALIO on Other Drugs

Table 8: Effect of TURALIO on Other Drugs
CYP3A Substrates
Clinical Impact | - TURALIO is a moderate CYP3A inducer. Concomitant use of TURALIO decreases the concentration of CYP3A substrates [see Clinical Pharmacology (12.3)], which may reduce the efficacy of these substrates.
Management | - Avoid coadministration of TURALIO with hormonal contraceptives [see Warnings and Precautions (5.3), Use in Specific Populations (8.3)]. - Avoid concomitant use of TURALIO with other CYP3A substrates, where minimal concentration changes may lead to serious therapeutic failures. If concomitant use is unavoidable, increase the CYP3A substrate dosage in accordance with approved product labeling.

8 USE IN SPECIFIC POPULATIONS

8.1 Pregnancy

Risk Summary

Based on findings from animal studies and its mechanism of action [see Clinical Pharmacology (12.1)], TURALIO may cause embryo-fetal harm when administered to a pregnant woman. The available human data do not establish the presence or absence of major birth defects or miscarriage related to the use of TURALIO. Oral administration of pexidartinib to pregnant animals during the period of organogenesis resulted in malformations, post-implantation loss, and abortion at maternal exposures that were approximately equal to the human exposure at the recommended dose (see Data). Advise pregnant women of the potential risk to a fetus.

In the U.S. general population, the estimated background risk of major birth defects and miscarriage in clinically recognized pregnancies is 2 to 4% and 15 to 20%, respectively.

Data

Animal Data

Embryo-fetal development studies investigating the administration of pexidartinib during the period of organogenesis were conducted in rats and rabbits. In rats, pexidartinib resulted in increased post-implantation loss and fetal malformations including localized fetal edema, absence of kidney and ureter, abnormalities of the reproductive tract, and developmental variations including misshapen kidney, decreased skeletal ossification and higher mean litter proportions of slightly or moderately malaligned sternebrae at doses of 40 mg/kg (approximately equal to the human exposure at the recommended dose). In rabbits, administration of pexidartinib resulted in increased post-implantation loss, abortion, and fetal malformations including absence of kidney or ureter, rudimentary, misshapen or malpositioned kidney, rib abnormalities, and skeletal variations of accessory skull bones at doses of 60 mg/kg (approximately equal to the human exposure at the recommended dose).

8.2 Lactation

Risk Summary

There are no data on the presence of pexidartinib or its metabolites in either human or animal milk or its effects on a breastfed child or on milk production. Because of the potential for serious adverse reactions in the breastfed child, advise women not to breastfeed during treatment with TURALIO and for at least 1 week after the final dose.

8.3 Females and Males of Reproductive Potential

TURALIO may cause fetal harm when administered to a pregnant woman [see Use in Specific Populations (8.1)].

Pregnancy Testing

Verify pregnancy status in females of reproductive potential prior to the initiation of TURALIO [see Use in Specific Populations (8.1)].

Contraception

Females

Advise females of reproductive potential to use effective non-hormonal contraception during treatment with TURALIO and for 1 month after the final dose. Counsel patients to use non-hormonal method(s) of contraception, since TURALIO can render hormonal contraceptives ineffective [see Drug Interactions (7.3), Nonclinical Toxicology (13.1)].

Males

Advise male patients with female partners of reproductive potential to use effective contraception during treatment with TURALIO and for 1 week after the final dose [see Nonclinical Toxicology (13.1)].

Infertility

Based on findings from animal studies, TURALIO may impair both male and female fertility [see Nonclinical Toxicology (13.1)].

8.4 Pediatric Use

The safety and effectiveness of TURALIO in pediatric patients have not been established.

8.5 Geriatric Use

Clinical studies of TURALIO did not include sufficient numbers of subjects aged 65 and over to determine whether they respond differently from younger subjects.

8.6 Renal Impairment

Reduce the dosage when administering TURALIO to patients with mild to severe renal impairment (CLcr 15 to 89 mL/min, estimated by Cockcroft-Gault [C-G]) [see Dosage and Administration (2.5), Clinical Pharmacology (12.3)].

8.7 Hepatic Impairment

No dosage adjustment is recommended for patients with mild hepatic impairment (total bilirubin ≤ upper limit of normal [ULN] with AST > ULN or total bilirubin >1 to 1.5 × ULN with any AST) [see Clinical Pharmacology (12.3)].

Reduce the dosage of TURALIO for patients with moderate hepatic impairment (total bilirubin >1.5 to 3 × ULN, not due to Gilbert's syndrome, with any AST) [see Dosage and Administration (2.6), Clinical Pharmacology (12.3)].

TURALIO has not been studied in patients with severe hepatic impairment (total bilirubin >3 to 10 × ULN and any AST).

10 OVERDOSAGE

Due to the high plasma protein binding, TURALIO is not expected to be dialyzable [see Clinical Pharmacology (12.3)].

11 DESCRIPTION

Pexidartinib is a kinase inhibitor. The chemical name of pexidartinib hydrochloride is 5-[(5-Chloro-1H-pyrrolo[2,3-b]pyridin-3-yl)methyl]-N-{[6-(trifluoromethyl)pyridin-3-yl]methyl}pyridin-2-amine monohydrochloride. Pexidartinib hydrochloride is an off-white to white solid. The molecular formula for pexidartinib hydrochloride is C20H15ClF3N5∙HCl. The molecular weight is 454.28 for the hydrochloride salt and 417.81 for the free base. The chemical structure is:

The solubility of pexidartinib hydrochloride in aqueous solutions decreases with increasing pH. The pKa1 and pKa2 were determined to be 2.6 and 5.4 respectively for the conjugate acids. Pexidartinib hydrochloride is soluble in methanol, slightly soluble in water and ethanol, and practically insoluble in heptane.

TURALIO (pexidartinib) capsules are for oral use. Each capsule contains 125 mg pexidartinib which is equivalent to 135.9 mg pexidartinib hydrochloride. The capsule contains the following inactive ingredients: poloxamer 407, mannitol, crospovidone, and magnesium stearate. The hypromellose capsule shell contains hypromellose, titanium dioxide and FD&C Blue No. 1.

12 CLINICAL PHARMACOLOGY

12.1 Mechanism of Action

Pexidartinib is a small molecule tyrosine kinase inhibitor that targets colony stimulating factor 1 receptor (CSF1R), KIT proto-oncogene receptor tyrosine kinase (KIT), and FMS-like tyrosine kinase 3 (FLT3) harboring an internal tandem duplication (ITD) mutation. Overexpression of the CSF1R ligand promotes cell proliferation and accumulation in the synovium. In vitro, pexidartinib inhibited proliferation of cell lines dependent on CSF1R and ligand-induced autophosphorylation of CSF1R. Pexidartinib also inhibited the proliferation of a CSF1R dependent cell line in vivo.

12.2 Pharmacodynamics

Exposure-Response Relationships

There is an exposure response relationship between pexidartinib steady state exposure and serum transaminase levels (ALT and AST) with a higher risk of increased serum transaminases at higher exposure. Additionally, increased transaminases occurred more frequently with higher pexidartinib doses between 200 to 1200 mg per day administered on an empty stomach (0.25 to 1.5 times the exposure from the recommended dose).

Cardiac Electrophysiology

At two times the mean maximum exposure of the recommended dosage, TURALIO does not prolong the QTc interval to any clinically relevant extent.

12.3 Pharmacokinetics

The pharmacokinetics of TURALIO was evaluated following single doses in healthy subjects and following multiple doses in patients as summarized in Table 9.

Table 9: TURALIO Exposure and Pharmacokinetic Parameters
General Information
Steady state exposure [Mean (SD)] [Pexidartinib 400 mg twice daily on an empty stomach (similar exposure to that of the recommended dosage)] | Cmax | 8625 (2746) ng/mL
Steady state exposure [Mean (SD)] [Pexidartinib 400 mg twice daily on an empty stomach (similar exposure to that of the recommended dosage)] | AUC0-12h | 77465 (24975) ng∙h/mL
Dose proportionality | Pexidartinib exposure (Cmax and AUC0-INF) increased linearly over the single oral dose range of 200 to 2400 mg administered on an empty stomach (0.5 to 6 times the exposure from the recommended dose).
Time to steady state [Estimated based on half life] | Approximately 7 days
Accumulation ratio (AUC) [Median] | 3.6
Absorption
Tmax [Median] | 2.5 hours
Effect of food
TURALIO 400 mg with a high-fat meal [The high-fat meal comprised 800 to 1000 calories with approximately 50% from fat (approximately 55 to 65 grams of total fat).] | Compared to an empty stomach:; - Increased pexidartinib Cmax and AUC0-INF by 100% - Delayed Tmax by 2.5 hours
TURALIO 400 mg with a low-fat meal [The low-fat meal comprised approximately 400 calories with 25% from fat (approximately 11 to 14 grams of total fat).] | Compared to an empty stomach:; - Increased pexidartinib Cmax by 56% and AUC0-INF by 59% - Delayed Tmax by 1.5 hours
Predicted relative AUC0-24h of TURALIO 250 mg with a low-fat meal to that of TURALIO 400 mg on an empty stomach | - No clinically significant difference
Distribution
In vitro plasma protein binding | - Greater than 99% - Human serum albumin: 99.9% - α-1 acid glycoprotein: 89.9%
Apparent volume of distribution (Vz/F) [Mean (CV%)] [After a single oral dose of pexidartinib] | - 187 L (27%)
Elimination
Apparent clearance [Mean (CV%)] | - 5.1 L/h (36%)
t1/2 [Mean (SD)] | - 26.6 (6.5) hours
Metabolism
Primary pathway | - Oxidation: CYP3A4 - Glucuronidation: UGT1A4
N-glucuronide metabolite | - Major inactive metabolite formed by UGT1A4 - Approximately 10% higher exposure than pexidartinib after a single dose
Excretion [After a single oral dose of radiolabeled pexidartinib]
 | - Feces: 65% (44% as unchanged) - Urine: 27% as metabolites (≥10% as N-glucuronide)

Specific Populations

No clinically meaningful differences in the pharmacokinetics of pexidartinib were observed based on age (18 to 84 years), sex, race (White and Black), or mild hepatic impairment (total bilirubin ≤ ULN with AST > ULN or total bilirubin > 1 to 1.5 × ULN with any AST).

Patients with Renal Impairment

Mild (CLcr 60 to 89 mL/min), moderate (CLcr 30 to 59 mL/min) and severe (CLcr 15 to 29 mL/min) renal impairment increased pexidartinib exposure (AUC) by approximately 30%, relative to that in patients with normal renal function (CLcr ≥90 mL/min).

Patients with Hepatic Impairment

Moderate hepatic impairment (total bilirubin > 1.5 to 3 × ULN, not due to Gilbert's syndrome, with any AST) increased pexidartinib exposure (AUC) by 43% relative to exposure in patients with normal hepatic function (total bilirubin and AST ≤ ULN).

The pharmacokinetics of pexidartinib have not been studied in patients with severe hepatic impairment (total bilirubin > 3 to 10 × ULN with any AST).

Drug Interaction Studies

Clinical Studies

Effects of Other Drugs on Pexidartinib

Strong or Moderate CYP3A Inducers: Coadministration of rifampicin (strong CYP3A inducer) decreased pexidartinib Cmax by 33% and AUC0-INF by 65%. Coadministration of efavirenz (moderate CYP3A inducer) is predicted to have no clinically significant differences in pexidartinib pharmacokinetics.

Strong or Moderate CYP3A Inhibitors: Coadministration of itraconazole (strong CYP3A inhibitor) increased pexidartinib Cmax by 48% and AUC0-INF by 70%. Coadministration of fluconazole (moderate CYP3A inhibitor) is predicted to increase pexidartinib Cmax by 41% and AUC by 67% at steady state.

UGT Inhibitors: Coadministration of probenecid (UGT inhibitor) increased pexidartinib AUC0-INF by 60% with no effect on Cmax.

Acid-Reducing Agents: Coadministration of esomeprazole (proton pump inhibitor) decreased pexidartinib Cmax by 55% and AUC0-INF by 50%. The effects of H2-receptor antagonists and locally-acting antacids on pexidartinib pharmacokinetics have not been studied.

Effects of Pexidartinib on Other Drugs

CYP3A Substrates: Coadministration of TURALIO at the approved recommended dosage decreased midazolam (CYP3A substrate) Cmax by 28% and AUC0-INF by 59%.

Other Drugs: When coadministered with omeprazole (CYP2C19 substrate), tolbutamide (CYP2C9 substrate), digoxin (P-gp substrate), or CYP2C8 substrate with TURALIO, no clinically significant differences in their pharmacokinetics were observed or predicted.

In Vitro Studies

CYP/UGT Enzymes: Pexidartinib inhibited and induced CYP2B6 at clinically relevant concentrations. Pexidartinib inhibited UGT1A1 at clinically relevant concentrations.

Transporters: Pexidartinib is not a substrate for P-gp, BCRP, OAT1, OAT3, OCT1, OCT2, OATP1B1, OATP1B3, OATP2B1, and BSEP.

Pexidartinib is an inhibitor of MATE1, MATE2-K, OATP1B1, OATP1B3 and OATP2B1.

13 NONCLINICAL TOXICOLOGY

13.1 Carcinogenesis, Mutagenesis, Impairment of Fertility

Carcinogenicity studies were performed in mice and rats. Both studies were negative for carcinogenic findings at exposures up to 9 times the human exposure at the recommended daily dose based on AUC.

Pexidartinib was not mutagenic in an in vitro bacterial reverse mutation (AMES) assay or clastogenic in either an in vitro human peripheral blood lymphocyte chromosomal aberrations assay or in an in vivo mouse bone marrow micronucleus assay.

Based on nonclinical findings, TURALIO may impair male and female fertility. In a fertility study in which pexidartinib was administered orally to male and female rats, there were reductions in pregnancy, as well as increases in pre- and post-implantation loss with a corresponding reduction in viable embryos at 40 mg/kg (approximately 1.3 times the human exposure at the recommended dose). Males at this dose level displayed reductions in spermatogenic parameters and adverse effects on sperm concentration, production, motility, and morphology. Lower testicular and epididymal weights occurred in this study at doses of ≥10 mg/kg/day (approximately 0.3 times the human exposure at the recommended dose). This is consistent with findings in chronic toxicology studies of germ cell depletion of the testes and hypospermia and cellular debris in the epididymis in male reproductive tissues of both rats and dogs at respective doses as low as 20 and 30 mg/kg/day (approximately 0.6 and 0.1 times the human exposure at the recommended dose). In rats, these changes persisted following a 16-week recovery period at the 60 mg/kg/day dose level (approximately 1.5 times the human exposure at the recommended dose).

In female rats, necrosis of corpora lutea occurred at doses ≥0.5 mg/kg/day (approximately 0.01 times the human exposure at the recommended dose) with pigment deposition within the interstitium of the ovaries, an increased incidence of luteal cysts and incidence/severity of hemorrhage of corpora lutea, and a decreased incidence of retained antral follicles and decreased corpora lutea at 60 mg/kg (approximately 1.8 times the human exposure at the recommended dose). In female dogs there were decreased follicle numbers and moderate atrophy of the oviduct, uterus, and cervix at doses as low as 1 mg/kg (approximately 0.01 times the human exposure at the recommended dose).

13.2 Animal Toxicology and/or Pharmacology

In repeat dose toxicity studies of up to 26 weeks in rats, there were findings of myxomatous change in the skin, tongue, and gastrointestinal tract, lymphoid depletion of the bone marrow and thymus, and chronic progressive nephropathy of the kidney at 20 mg/kg/day (approximately 0.6 times the human exposure at the recommended dose). Similar changes occurred in the rat carcinogenicity study along with alterations in the tunica intima of the aorta. Vascular inflammation consistent with polyarteritis nodosa occurred in male rats at 60 mg/kg/day (approximately 1.5 times the human exposure at the recommended dose). There were also dose-dependent findings of minimal to moderate subphyseal or cortical hyperostosis and physeal hypertrophy in the femur that correlated with decreased systemic phosphate levels at doses ≥ 60 mg/kg.

14 CLINICAL STUDIES

14.1 Tenosynovial Giant Cell Tumor

The efficacy of TURALIO 250 mg orally twice daily administered with a low-fat meal has been established based on adequate and well-controlled studies of TURALIO 400 mg orally twice daily administered on an empty stomach and additional pharmacokinetic data that indicate there is no clinically significant difference in the relative exposure between the two dosages.

The efficacy of TURALIO was evaluated in ENLIVEN (NCT02371369), a double-blind, randomized (1:1), placebo-controlled, multicenter trial in patients with symptomatic TGCT [also referred to as giant cell tumor of the tendon sheath (GCT-TS) or pigmented villonodular synovitis (PVNS)] for whom surgical removal of the tumor would be associated with worsening functional limitation or severe morbidity. Eligible patients were required to have measurable disease per the Response Evaluation Criteria in Solid Tumors (RECIST) v1.1. Patients were randomized to placebo or TURALIO administered on an empty stomach: 400 mg in the morning and 600 mg in the evening for 2 weeks followed by 400 mg twice daily until unacceptable toxicity or disease progression. Randomization was stratified by geographic region (US vs. non-US countries) and disease location (upper extremity vs. lower extremity involvement). Patients who completed treatment in the double-blind, randomized part of the trial were eligible to advance to an open-label extension part in which all patients were given the option to receive pexidartinib.

The major efficacy outcome measure was overall response rate (ORR) as assessed by blinded independent central review (BICR) at Week 25 using RECIST v1.1. Additional efficacy outcome measures were mean change from baseline in range of motion of the affected joint at Week 25 and ORR as assessed by BICR at Week 25 using tumor volume score (TVS). Range of motion was measured as a percent of normal reference range for the affected joint. Range of motion assessments were performed by a third-party clinical assessor using a goniometer. TVS was defined in ENLIVEN as the estimated volume of the maximally distended synovial cavity or tendon sheath involved, measured in 10% increments. Patients in the placebo arm were offered TURALIO at Week 25 beginning with a 400 mg twice daily dose, as permitted by the study protocol.

A total of 120 patients were randomized, 61 to the TURALIO arm and 59 to the placebo arm. The median age was 44 years (range: 18-79); 59% were females; 88% were White; 53% had prior surgery; 88% were diagnosed with diffuse TGCT; and 9% had previously been treated with systemic therapy. Disease locations were knee (61%), ankle (18%), hip (11%), wrist (3%), foot (3%) and other (5%).

ENLIVEN demonstrated a statistically significant improvement in ORR in patients randomized to TURALIO compared with placebo. Efficacy results are summarized in Table 10.

Table 10: Efficacy Results Assessed at Week 25 for ENLIVEN
Efficacy Parameter | TURALIO N=61 | Placebo N=59
Overall Response Rate (ORR) [Blinded independent central review] , [Data cut-off date January 31, 2018]
ORR (95% CI) | 38% (27%, 50%) | 0 (0, 6%)
Complete Response | 15% | 0
Partial Response | 23% | 0
P-value [Fisher's exact test] | <0.0001
Duration of Response (DOR)
Range (months) | 6.9+, 24.9+ | NA
CI: confidence interval; NA: not applicable; SD: standard deviation; LS: least squares; +: denotes ongoing at last assessment

The analysis of mean change from baseline in range of motion at Week 25 demonstrated a statistically significant improvement in patients randomized to TURALIO compared to placebo. Figure 1 shows the change from baseline in range of motion for each patient at Week 25 (TURALIO N=45, placebo N=43). Results were excluded for 1 patient with missing baseline and 31 patients with a missing range of motion assessment at Week 25.

Figure 1: Change from Baseline in Range of Motion at Week 25 for ENLIVEN

ORR by TVS was 56% (95% CI: 43%, 67%) in patients randomized to the TURALIO arm and 0% in patients randomized to the placebo arm; p < 0.0001.

At completion of the open-label extension part of the study in which all patients received TURALIO, the ORR using RECIST v1.1 was 61% (95% CI: 48%, 72%) in the 61 patients originally randomized to the TURALIO arm. The median duration of response was not reached (range: 4.6+, 63.4+ months) in the 37 responders.

16 HOW SUPPLIED/STORAGE AND HANDLING

TURALIO 125 mg capsules are supplied as size 1 with white opaque body and powder blue opaque cap with black print "DSC521", available in:

- 28 count bottle
- 120 count bottle

NDC#: 65597-407-28
NDC#: 65597-407-20

STORAGE AND HANDLING

Store at 20°C to 25°C (68°F to 77°F); excursions permitted to 15°C to 30°C (59°F to 86°F) [see USP Controlled Room Temperature].

Keep containers closed and do not remove desiccant from bottles.

17 PATIENT COUNSELING INFORMATION

Advise the patient to read the FDA-approved patient labeling (Medication Guide).

Hepatotoxicity

Advise patients of the risk of hepatotoxicity that could be fatal and that they will need to undergo monitoring for liver injury. Advise patients to immediately report any signs or symptoms of severe liver injury to their healthcare provider and that liver testing and prompt cessation of TURALIO may not eliminate the risk of severe or life-threatening liver injury [see Warnings and Precautions (5.1)].

TURALIO REMS Program

- TURALIO is available only through a restricted program called TURALIO REMS Program and patients are required to be part of the patient registry [see Warnings and Precautions (5.2)].
- TURALIO is available only from certified pharmacies participating in the program. Therefore, provide patients with the telephone number and website for information on how to obtain the product.

Embryo-Fetal Toxicity

- Advise pregnant women and females of reproductive potential of the potential risk to a fetus. Advise females of reproductive potential to inform their healthcare provider of a known or suspected pregnancy [see Warnings and Precautions (5.3), Use in Specific Populations (8.1, 8.3)].
- Advise females of reproductive potential to use effective non-hormonal contraception during treatment with TURALIO and for 1 month after the final dose [see Drug Interactions (7.3), Use in Specific Populations (8.3)].
- Advise male patients with female partners of reproductive potential to use effective contraception during treatment and for 1 week after the final dose [see Use in Specific Populations (8.3), Nonclinical Toxicology (13.1)].

Lactation

Advise females not to breastfeed during treatment with TURALIO and for 1 week after the final dose [see Use in Specific Populations (8.2)].

Infertility

Advise females and males of reproductive potential that TURALIO may impair fertility [see Use in Specific Populations (8.3), Nonclinical Toxicology (13.1)].

Administration

- Instruct patients to take TURALIO with a low-fat meal (approximately 11 to 14 grams of total fat) and to avoid taking TURALIO with a high-fat meal (approximately 55 to 65 grams of total fat). Consider referring patients to a dietician as deemed necessary [see Dosage and Administration (2.1), Warnings and Precautions (5.4), Drug Interactions (7.2)].
- Instruct patients to swallow capsules whole (do not open, break, or chew) [see Dosage and Administration (2.1)].

Drug Interactions

Advise patients to inform their healthcare providers of all concomitant products, including over-the-counter products and supplements [see Dosage and Administration (2), Drug Interactions (7)].

Photosensitivity

Inform patients of the signs and symptoms of photosensitivity. Advise patients to avoid prolonged sun exposure and to use sunscreen and protective clothing during treatment with TURALIO [see Adverse Reactions (6.1)].

Manufactured for: Daiichi Sankyo, Inc.
Basking Ridge, NJ 07920

TURALIO® is a registered trademark of Daiichi Sankyo Company, Limited.
©2025, Daiichi Sankyo, Inc.

USPI-TUR125-C8-0125-r102

Medication Guide
TURALIO® (tur-a-lee-oh)
(pexidartinib)
capsules

What is the most important information I should know about TURALIO?
TURALIO can cause serious side effects, including:
Serious liver problems which may be severe and can lead to death, including liver failure and a liver injury called vanishing bile duct syndrome (VBDS) that can cause the loss of bile ducts in the liver. Severe or life-threatening liver problems can happen with TURALIO even if your healthcare provider monitors liver blood tests during treatment and stops treatment with TURALIO.
Your healthcare provider will do blood tests to check for liver problems:

- before starting treatment with TURALIO,
- every week for the first 8 weeks during treatment,
- every 2 weeks for the next month,
- then, every 3 months after that.

If you develop liver problems during treatment with TURALIO, your healthcare provider may do blood tests more often to monitor you or refer you to a liver specialist (hepatologist). It is important to stay under the care of your healthcare provider during treatment with TURALIO.
Stop taking TURALIO and call your healthcare provider right away if you develop:

- yellowing of your skin and whites of your eyes
- dark urine

Tell your healthcare provider right away if you have any of these symptoms of liver problems during treatment with TURALIO:

- lack or loss of appetite
- right upper stomach-area (abdomen) pain or tenderness
- feeling overly tired
- nausea

- vomiting
- fever
- rash
- itching

TURALIO Risk Evaluation and Mitigation Strategy (REMS). Because of the risk of serious liver problems, TURALIO is available only through a restricted program called the TURALIO REMS Program. Your healthcare provider must be enrolled in the program in order for you to be prescribed TURALIO. There is a registry that collects information about the effects of taking TURALIO over time. You must complete and sign an enrollment form for the TURALIO REMS Program and the registry. Ask your healthcare provider for more information.
See "What are the possible side effects of TURALIO?" for more information about side effects.

What is TURALIO?
TURALIO is a prescription medicine used to treat certain adults who have tenosynovial giant cell tumor (TGCT) that is not likely to improve with surgery. TGCT is also known as giant cell tumor of the tendon sheath (GCT-TS) or pigmented villonodular synovitis (PVNS).
It is not known if TURALIO is safe and effective in children.

Before taking TURALIO, tell your healthcare provider about all of your medical conditions, including if you:

- have or had liver problems.
- have kidney problems.
- are pregnant or plan to become pregnant. TURALIO may harm your unborn baby.
  If you are a female who is able to become pregnant:
  - Your healthcare provider will do a pregnancy test before you start treatment with TURALIO.
  - Females who are able to become pregnant should use effective non-hormonal birth control (contraception) during treatment with TURALIO and for 1 month after your final dose of TURALIO. Birth control pills (oral contraceptives) and other hormonal forms of birth control may not be effective if used during treatment with TURALIO. Talk with your healthcare provider about birth control methods you can use during this time.
  - Tell your healthcare provider right away if you become pregnant or think you are pregnant during treatment with TURALIO.
  If you are a male with a female partner who is able to become pregnant:
  - Use effective birth control (contraception) during treatment and for 1 week after your final dose of TURALIO.
  - Tell your healthcare provider right away if your female partner becomes pregnant or thinks she is pregnant during your treatment with TURALIO.
- are breastfeeding or plan to breastfeed. Do not breastfeed during treatment with TURALIO and for at least 1 week after your final dose of TURALIO.

Tell your healthcare provider about all the medicines you take, including prescription and over-the-counter medicines, vitamins, and herbal supplements. Certain medicines may affect the way TURALIO works and TURALIO may affect how other medicines work. Taking TURALIO with certain medicines may increase the amount of TURALIO in your blood. This may make it more likely for you to develop side effects and may cause more severe side effects.

- Avoid taking the following medicines or supplements during treatment with TURALIO because they can affect how TURALIO works:
  - Proton Pump Inhibitor medicines (PPIs)
  - St. John's wort

How should I take TURALIO?

- Your healthcare provider will explain to you how you will receive your TURALIO.
- Take TURALIO exactly as your healthcare provider tells you to.
- TURALIO is usually taken 2 times a day. Your healthcare provider will tell you how much TURALIO to take and when to take it.
- Take TURALIO with a low-fat meal (about 11 to 14 grams of total fat). Taking TURALIO with a high-fat meal increases the amount of TURALIO in your blood. This may make it more likely for you to develop side effects and may cause more severe side effects, including serious liver problems. See "What are the possible side effects of TURALIO?"
  - Talk with your healthcare provider about examples of foods that you can eat for a low-fat meal that contains about 11 to 14 grams of total fat.
  - Your healthcare provider may refer you to a dietician, if needed.
- Swallow TURALIO capsules whole.
- Do not open, break, or chew TURALIO capsules.
- If you need to take an acid-reducing medicine, follow your healthcare provider's instructions for which medicine to take and when to take it.
  - If you take an antacid medicine: Take TURALIO either 2 hours before or 2 hours after taking an antacid medicine.
  - If you take an H2 receptor blocker medicine: Take TURALIO at least 2 hours before or 10 hours after taking an H2 receptor blocker medicine.
- Tell your healthcare provider about all the medicines you take. See the section "Before taking TURALIO, tell your healthcare provider about all of your medical conditions, including if you:"
- If you vomit after taking a dose, or if you miss a dose of TURALIO, take your next dose at your regular time.

What should I avoid while taking TURALIO?

- Avoid grapefruit or drinking grapefruit juice during treatment with TURALIO. Grapefruit or grapefruit juice can cause you to have too much TURALIO in your blood and may lead to increased side effects and more severe side effects.
- Avoid spending prolonged time in sunlight. TURALIO can make your skin sensitive to the sun (photosensitivity), and you may burn more easily. You should use sunscreen and wear protective clothing that covers your skin to help protect against sunburn if you have to be in the sunlight during treatment with TURALIO.

What are the possible side effects of TURALIO?
TURALIO can cause serious side effects.

- See "What is the most important information I should know about TURALIO?"
- There are possible risks if TURALIO is taken with a high-fat meal. Avoid taking TURALIO with a high-fat meal (about 55 to 65 grams of total fat). Taking TURALIO with a high-fat meal increases the amount of medicine in your blood. This may make it more likely for you to develop side effects and may cause more severe side effects, including serious liver problems. Take TURALIO with a low-fat meal (about 11 to 14 grams of total fat). See "How should I take TURALIO?"

The most common side effects of TURALIO include:

- changes in blood liver tests
- hair color changes
- tiredness
- increased cholesterol level in your blood

- decreased white blood cells and red blood cells
- swelling in or around your eyes
- rash, itching, hives, skin redness, and acne
- loss of taste or changes in the way things taste
- decreased phosphate in your blood

TURALIO may affect fertility in females and males, which may affect your ability to have children. Talk to your healthcare provider if you have concerns about fertility.
These are not all of the possible side effects of TURALIO.
Call your doctor for medical advice about side effects. You may report side effects to FDA at 1-800-FDA-1088.

How should I store TURALIO?

- Store TURALIO at room temperature between 68°F to 77°F (20°C to 25°C).
- Keep the TURALIO container closed tightly.
- TURALIO comes with a drying agent (desiccant) in the container. Keep the desiccant in the container.

Keep TURALIO and all medicines out of the reach of children.

General information about the safe and effective use of TURALIO
Medicines are sometimes prescribed for purposes other than those listed in a Medication Guide. Do not use TURALIO for a condition for which it was not prescribed. Do not give TURALIO to other people, even if they have the same symptoms that you have. It may harm them. You can ask your pharmacist or healthcare provider for information about TURALIO that is written for health professionals.

What are the ingredients in TURALIO?
Active Ingredient: pexidartinib
Inactive Ingredients: poloxamer 407, mannitol, crospovidone, and magnesium stearate. Capsule shell: hypromellose, titanium dioxide, and FD&C Blue No. 1
Manufactured for: Daiichi Sankyo, Inc., Basking Ridge, NJ 07920
TURALIO® is a registered trademark of Daiichi Sankyo Company, Limited. ©2025, Daiichi Sankyo, Inc.
USMG-TUR125-C8-0125-r102
For more information, call 1-877-437-7763 or go to https://www.turalio.com.

This Medication Guide has been approved by the U.S. Food and Drug Administration.

Revised: 1/2025

PRINCIPAL DISPLAY PANEL - 125 mg Capsule Bottle Carton

NDC 65597-407-20
Rx only

Turalio®
(pexidartinib)
capsules

125 mg

120 capsules

Take with a low-fat meal.

Pharmacist: Dispense the
Medication Guide to each patient.

Daiichi-Sankyo

PRINCIPAL DISPLAY PANEL - 125 mg Capsule Bottle Carton - 65597-407-28

NDC 65597-407-28
Rx only

Turalio®
(pexidartinib)
capsules

125 mg

28 capsules

Take with a low-fat meal.

Pharmacist: Dispense the
Medication Guide to each patient.

Daiichi-Sankyo